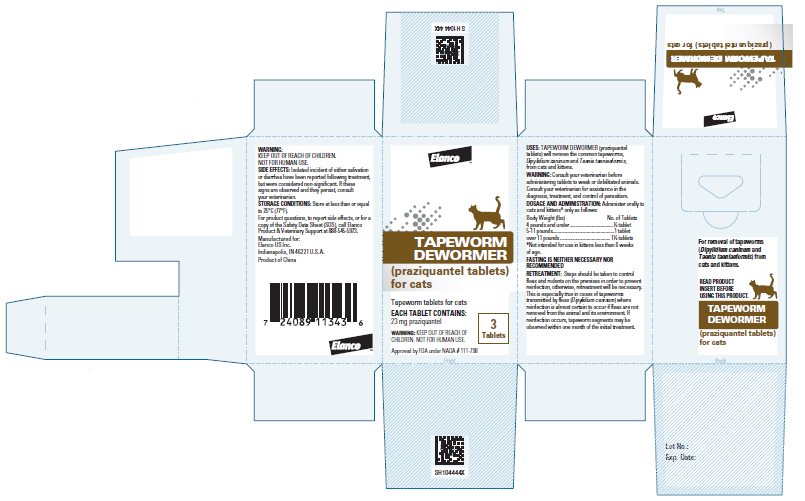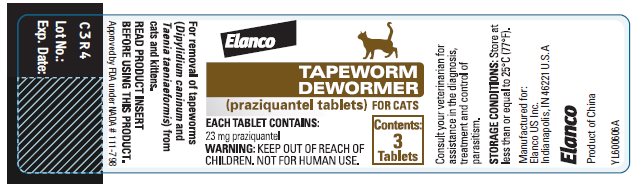 DRUG LABEL: Tapeworm Dewormer for Cats
NDC: 58198-0063 | Form: TABLET
Manufacturer: Elanco US Inc.
Category: animal | Type: OTC ANIMAL DRUG LABEL
Date: 20260223

ACTIVE INGREDIENTS: PRAZIQUANTEL 23 mg/1 1

Elanco™
Tapeworm Dewormer
(praziquantel tablets) for cats

Consult your veterinarian for assistance in the diagnosis, treatment and control of parasitism. Consult your veterinarian before administering the tablets to weak or debilitated animals.

Each tablet contains 23 mg praziquantel.

DESCRIPTION:

Tapeworm Dewormer (praziquantel tablets) are sized for easy oral administration to either adult cats or kittens. The tablets may be crumbled and mixed with the feed.

USES:

TAPEWORM DEWORMER (praziquantel tablets) will remove the common tapeworms, Dipylidium caninum and Taenia taeniaeformis, from cats and kittens.

DOSAGE AND ADMINISTRATION:

Tapeworm Dewormer (praziquantel tablets) may be given directly in the mouth or crumbled and mixed with the food. Administer to cats and kittens* only as follows:

Body Weight (lbs) | No. of Tablets
4 pounds and under | ½ tablet
5-11 pounds | 1 tablet
Over 11 pounds | 1 ½ tablets
*Not intended for use in kittens less than 6 weeks of age.

FASTING IS NEITHER NECESSARY NOR RECOMMENDED.

RETREATMENT:

Steps should be taken to control fleas and rodents on the premises in order to prevent reinfection; otherwise, retreatment will be necessary. This is especially true in cases of tapeworms transmitted by fleas (Dipylidium caninum) where reinfection is almost certain to occur if fleas are not removed from the animal and its environment. If reinfection occurs, tapeworm segments may be observed within one month of the initial treatment.

SIDE EFFECTS:

Isolated incident of either salivation or diarrhea have been reported following treatment, but were considered non-significant. If these signs are observed and they persist, consult your veterinarian.

Questions?

For product questions, to report side effects, or for a copy of the Safety Data Sheet (SDS), call Elanco Product & Veterinary Support at 888-545-5973.

For additional information about reporting side effects for animal drugs, contact FDA at 1-888-FDA-VETS or http://www.fda.gov/reportanimalae.

WARNING:

Keep out of the reach of children. Not for human use.

HOW SUPPLIED:

Bottle of 3 scored tablets. Each scored tablet contains 23 mg praziquantel.

STORAGE CONDITIONS:

Store at less than or equal to 25°C (77°F).

Elanco™
Manufactured for:
Elanco US Inc.
Indianapolis, IN 46221 U.S.A
Approved by FDA under NADA # 111-798

Elanco and the diagonal bar logo are trademarks of Elanco or its affiliates.

Product of China November 2025

PA104444X

© 2025 Elanco or its affiliates

Principal Display Panel - 23 mg Carton Label

ElancoTM

TAPEWORM
DEWORMER

(praziquantel tablets)
for cats

Tapeworm tablets for cats
EACH TABLET CONTAINS:
23 mg praziquantel

WARNING: KEEP OUT OF REACH OF
CHILDREN. NOT FOR HUMAN USE.

3
Tablets

Approved by FDA under NADA # 111-798

Principal Display Panel – 23 mg Bottle Label

Elanco

TAPEWORM
DEWORMER

(praziquantel tablets) FOR CATS

EACH TABLET CONTAINS:

23 mg praziquantel

WARNING: KEEP OUT OF REACH OF
CHILDREN. NOT FOR HUMAN USE.

Contents:
3
Tablets